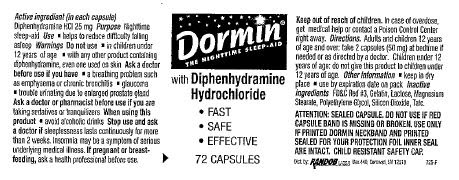 DRUG LABEL: Dormin
NDC: 52412-100 | Form: CAPSULE
Manufacturer: Randob Labs,Ltd.
Category: otc | Type: HUMAN OTC DRUG LABEL
Date: 20190412

ACTIVE INGREDIENTS: DIPHENHYDRAMINE HYDROCHLORIDE 25 mg/1 1
INACTIVE INGREDIENTS: FD&C RED NO. 3; GELATIN, UNSPECIFIED; LACTOSE, UNSPECIFIED FORM; MAGNESIUM STEARATE; POLYETHYLENE GLYCOL 8000; SILICON DIOXIDE; TALC

Drug Facts

Active ingredient

Diphenhydramine Hydrochloride

Keep out of reach of children. In case of overdose, get medical help or contact a Poison Control Center right away.

Uses

- helps to reduce difficulty falling asleep

Warnings

- Do not use
- in children under 12 years of age
- with any other product containing diphenhydramine, even one used on skin

Ask Doctor

As a doctor before use if you have

- a breathing problem such as emphysema or chronic bronchitis
- glaucoma
- trouble urinating due to enlarged prostate gland

Ask Doctor/Pharmacist

As a doctor or pharmacist before use if you are taking sedatives or tranquilizers

When Using

When using this product

- avoid alcoholic drinks

Stop Use

Stop use and ask a doctor if sleeplessness lasts for more than 2 weeks. Insomnia may be a symptom of serious underlying medical illness.

Pregnancy or Breast Feeding

If pregnant or breast-feeding, ask a health professional before use.

Directions

Adult and children 12 years and over: Take 2 capsules (50 mg) at bedtime if needed or as directed by a doctor

Children under 12 years of age: Do not give this product to children under 12 years of age

Other Information

- keep in dry place

Use by expiration date on pack

Inactive Ingredients

FD&C Red No. 3, Gelatin, Lactose, Magnesium Stearate, Polyethylene Glycol, Silicon Dioxide, Talc.

Principal Display Panel

Dormin®

THE NIGHTTIME SLEEP-AID

With Diphenhydramine Hydrochloride

- FAST
- SAFE
- EFFECTIVE

72 Capsules